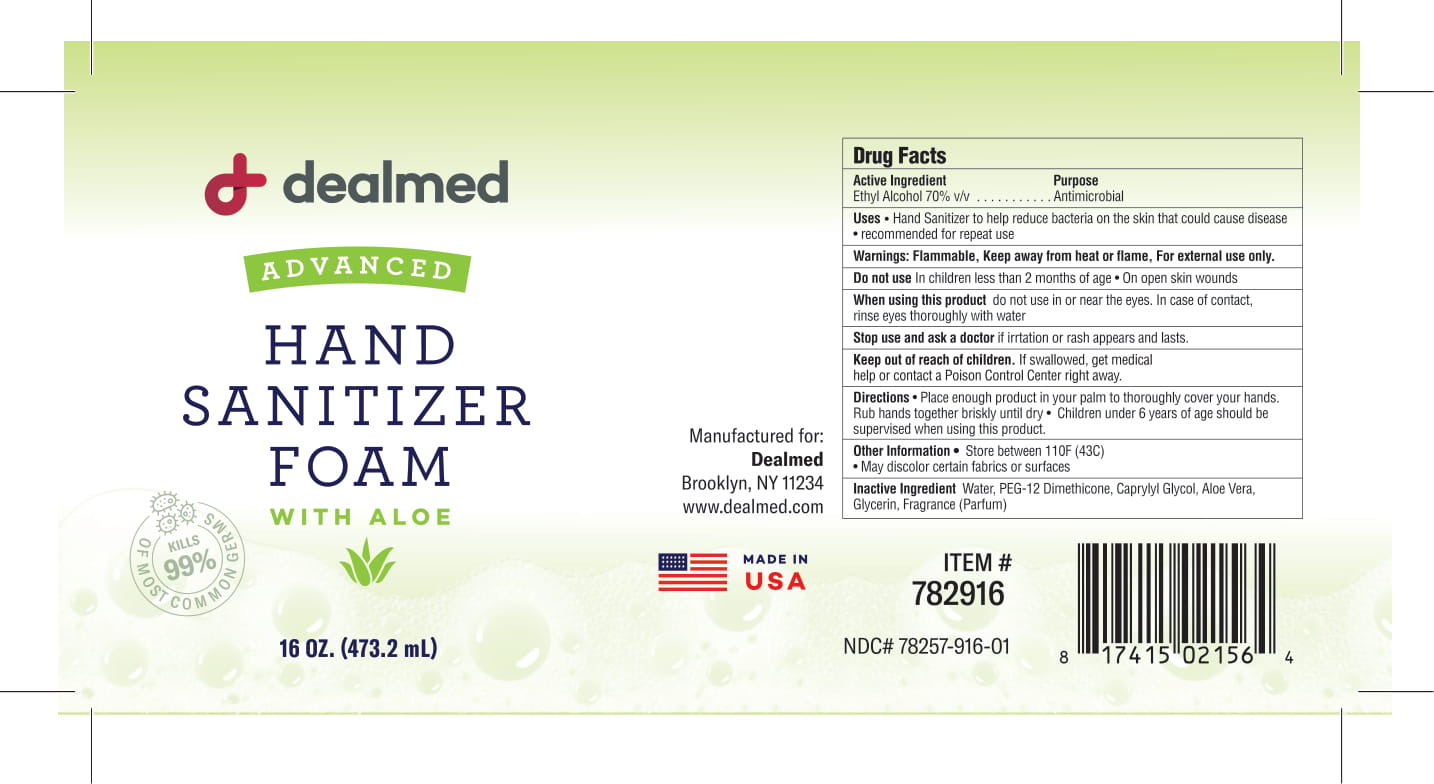 DRUG LABEL: Advanced Hand Sanitizer Foam with Aloe
NDC: 78257-916 | Form: SOLUTION
Manufacturer: DEALMED MEDICAL SUPPLIES LLC
Category: otc | Type: HUMAN OTC DRUG LABEL
Date: 20220206

ACTIVE INGREDIENTS: ALCOHOL 70 mL/100 mL
INACTIVE INGREDIENTS: PEG-12 DIMETHICONE; ALOE VERA LEAF; FRAGRANCE CLEAN ORC0600327; CAPRYLYL GLYCOL; GLYCERIN; WATER

Active Ingredient(s)

Ethyl Alcohol 70% v/v. Purpose: Antiseptic

Purpose

Antiseptic, Hand Sanitizer

Use

Hand Sanitizer to help reduce bacteria on the skin that can cause disease. recommended for repeat use

Warnings

Flammable. Keep away from heat or flame, For external use only.

Do not use

- In children less than 2 months of age
- On open skin wounds

Do not use in or near the eyes. in case of contact, rinse thoroughly with water.

Stop use and ask a doctor if irritation or rash appears and lasts.

Keep out of reach of children. If swallowed, get medical help, or contact a Poison Control Center right away.

Directions

- Place enough product in your palm to thorougly cover your hands. Rub hands together until dry.
- Children under 6 years of age should be supervised when using this product.

Other information

- Store below 110FC (43C).
- May discolor certain fabrics or surfaces.

Inactive ingredients

Water, PEG-12 Dimethicone, Carprylyl Glycol, Aloe Vera, Glycerin, Fragrance

Package Label - Principal Display Panel

473.2 mL NDC: 78257-916-01